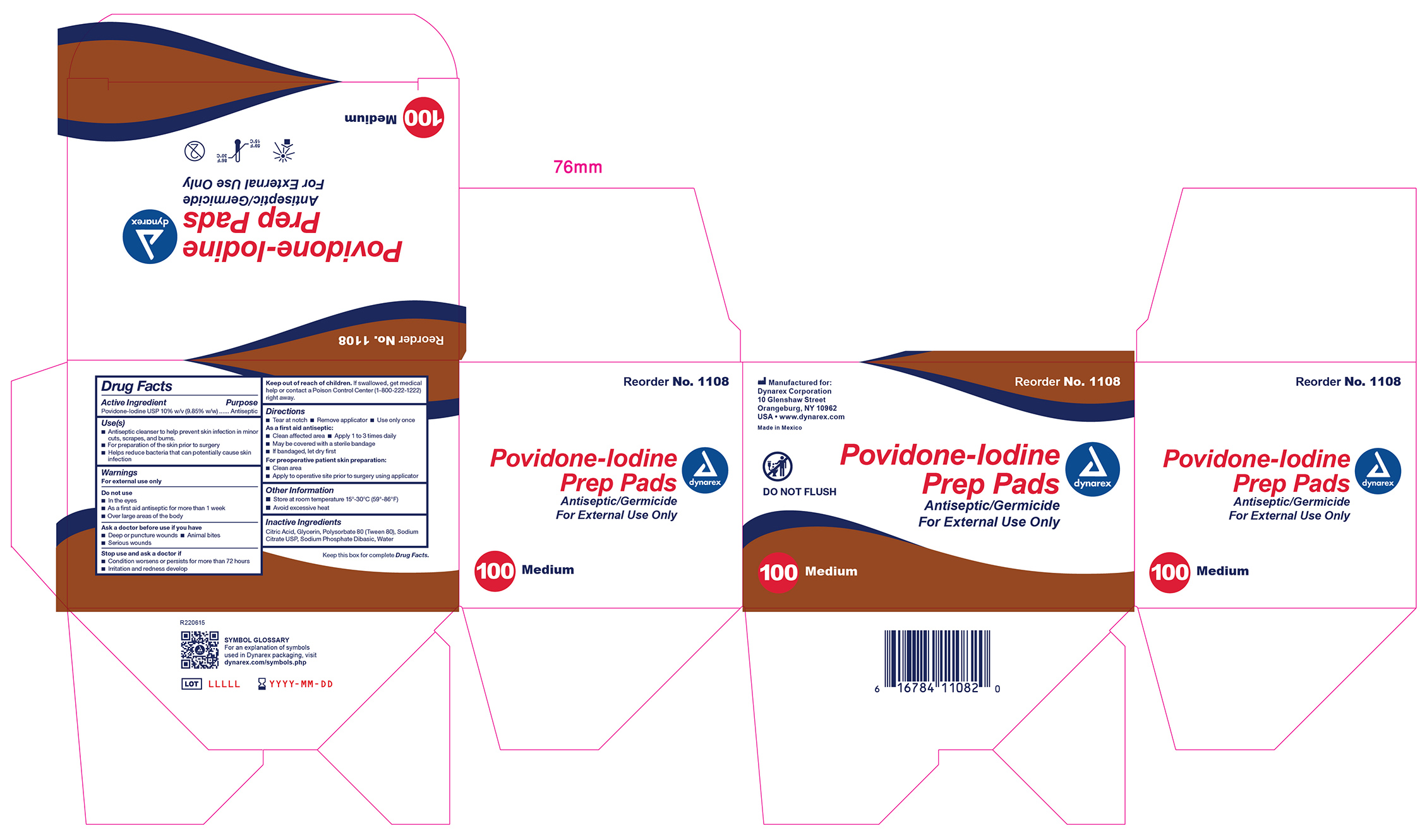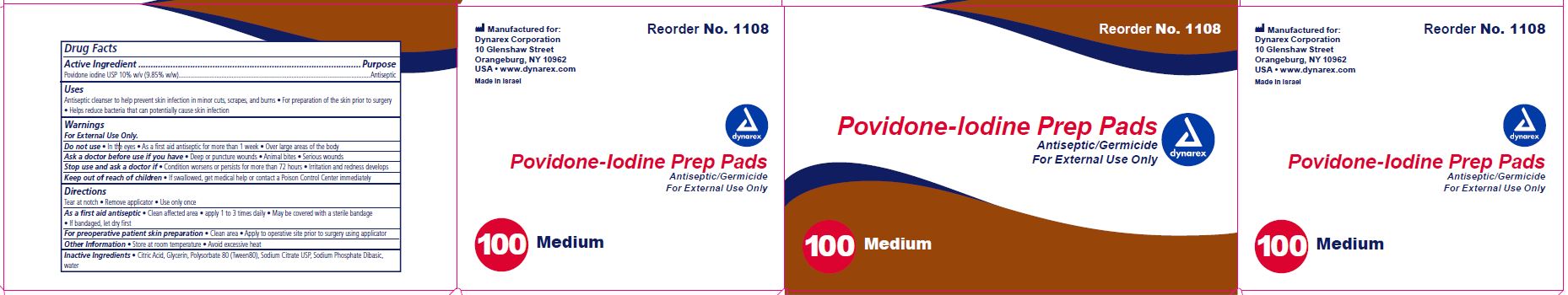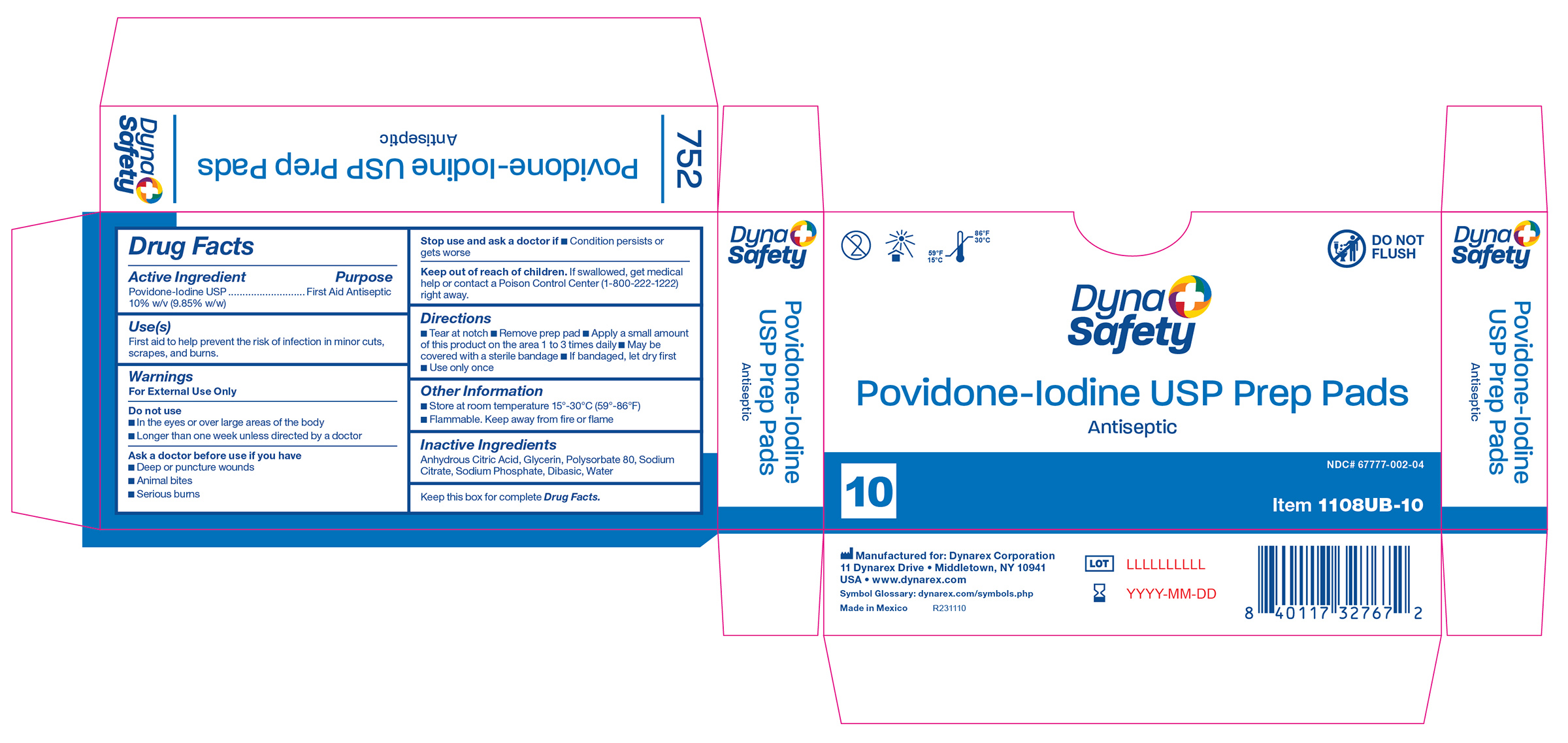 DRUG LABEL: Povidone Iodine Prep Pad
NDC: 67777-002 | Form: SWAB
Manufacturer: Dynarex Corporation
Category: otc | Type: HUMAN OTC DRUG LABEL
Date: 20240718

ACTIVE INGREDIENTS: POVIDONE-IODINE 10 g/100 g
INACTIVE INGREDIENTS: GLYCERIN; WATER; POLYSORBATE 80; SODIUM CITRATE; SODIUM PHOSPHATE, DIBASIC; ANHYDROUS CITRIC ACID

1108 Povidone Iodine Prep Pad NDC 67777-002-01
1108UB-10 Povidone Iodine Prep Pad NDC 67777-002-03

Active Ingredient

Povidone-Iodine USP 10% w/v (9.85% w/w)

Purpose

First Aid Antiseptic

Use(s)

First aid to help prevent the risk of infection in minor cuts, scrapes, and burns

Warnings

For External Use Only

Do not use

• In the eyes or over large areas of the body

• Longer than one week unless directed by a doctor

Ask a doctor before use if you have

• Deep or puncture wounds

• Animal bites

• Serious burns

Stop use and ask a doctor if

• Condition persists or gets worse

Keep out of reach of children

If swallowed, get medical help or contact a Poison Control Center (1-800-222-1222) right away.

Directions

- Tear at notch
- Remove prep pad
- Apply a small amount of this product on the area 1 to 3 times daily.
- May be covered with a sterile bandage
- If bandaged, let dry first
- Use only once

Other Information

- Store at room temperature 15º-30ºC (59º-86ºF)
- Flammable. Keep away from fire or flame

Inactive Ingredients

Anhydrous Citric Acid, Glycerin, Polysorbate 80, Sodium Citrate USP, Sodium Phosphate Dibasic, Water

Label

Povidon Iodine Prep Pad

Label 1108UB-10

1108UB-10